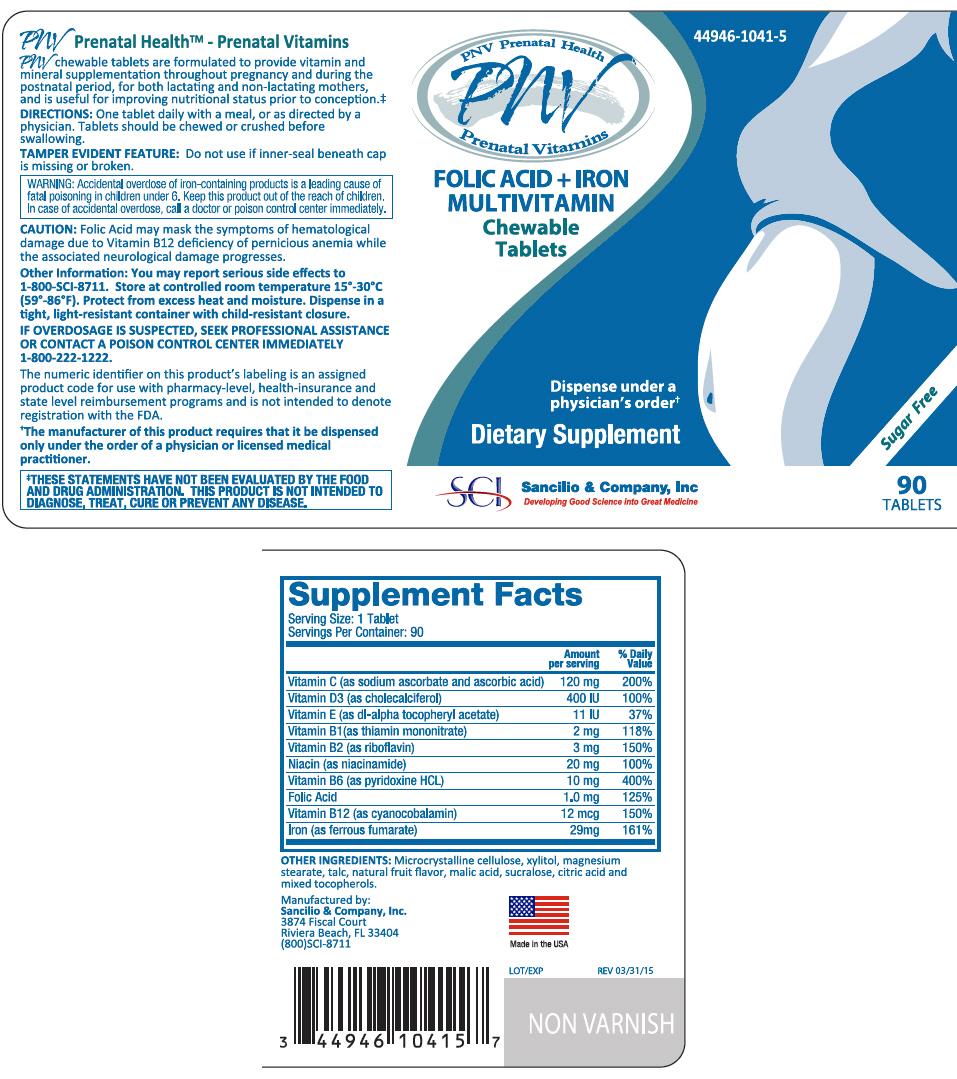 DRUG LABEL: PNV Prenatal Vitamin
NDC: 44946-1041 | Form: TABLET, CHEWABLE
Manufacturer: Sancilio & Company Inc
Category: other | Type: DIETARY SUPPLEMENT
Date: 20171227

ACTIVE INGREDIENTS: .Alpha.-Tocopherol Acetate, DL- 11 [iU]/1 1; Cholecalciferol 400 [iU]/1 1; Cyanocobalamin 12 ug/1 1; Ferrous fumarate 29 mg/1 1; Folic Acid 1 mg/1 1; Niacinamide 20 mg/1 1; Sodium Ascorbate 60 mg/1 1; Ascorbic Acid 60 mg/1 1; Pyridoxine Hydrochloride 10 mg/1 1; Riboflavin 3 mg/1 1; Thiamine Mononitrate 2 mg/1 1
INACTIVE INGREDIENTS: Xylitol; Microcrystalline Cellulose; Malic Acid; Talc; Magnesium stearate; Sucralose; Anhydrous Citric Acid; Tocopherol

PNV Prenatal Health™ - Prenatal Vitamins

STATEMENT OF IDENTITY

PNV Chewable Tablets are formulated to provide vitamin and mineral supplementation throughout pregnancy and during the postnatal period, for both the lactating and non-lactating mothers, and is useful for improving nutritional status prior to conception.

STATEMENT OF IDENTITY

Each fruit-flavored PNV Chewable tablet contains:

VITAMINS:
Vitamin C (as sodium ascorbate and ascorbic acid) | 120 mg
Vitamin D3 (as cholecalciferol) | 400 IU
Vitamin E (as dl-alpha tocopheryl acetate) | 11 IU
Vitamin B1 (as thiamin mononitrate) | 2 mg
Vitamin B2 (as riboflavin) | 3 mg
Vitamin B3 (as niacinamide) | 20 mg
Vitamin B6 (as pyridoxine HCL) | 10 mg
Vitamin Folic Acid | 1 mg
Vitamin B12 (as cyanocobalamin) | 12 mcg
MINERAL:
Iron (as ferrous fumarate) | 29 mg

OTHER INGREDIENTS

Microcrystalline cellulose, xylitol, magnesium stearate, talc, natural fruit flavor, malic acid, sucralose, citric acid, and mixed tocopherols.

DIRECTIONS

One tablet daily with a meal, or as directed by a physician. Tablets should be chewed or crushed before swallowing.

CAUTION

Folic acid may partially correct the hematological damage due to vitamin B12 deficiency of pernicious anemia, while the associated neurological damage progresses.

WARNING

Accidental overdose of iron-containing products is a leading cause of fatal poisoning in children under 6. Keep this product out of the reach of children. In case of accidental overdose, call a doctor or poison control center immediately.

ADVERSE REACTIONS

In some cases, allergic hypersensitivity has been reported following administration of folic acid. Mild gastrointestinal disturbances may occur with products containing ferrous fumarate (iron), but usually subside with continuation of therapy.

HOW SUPPLIED

PNV Prenatal Health™ - Prenatal Vitamins are light brown to brown-speckled, fruit-flavored, round tablets debossed "SCI" on one side.

STORAGE AND HANDLING

STORE AT CONTROLLED ROOM TEMPERATURE 15°-30°C (59°-86°F).

PROTECT FROM EXCESS HEAT AND MOISTURE. Dispense in a tight, light-resistant container with child-resistant closure.

HEALTH CLAIM

This medical food product is formulated to be administered orally, under the supervision of a physician and is intended for the management of a dietary deficiency of folic acid and iron for which a distinctive nutritional requirement, based on recognized scientific principles, has been established by medical evaluation. The numeric identifier on this product's labeling is an assigned product code for use with pharmacy-level, health insurance and state level reimbursement programs and is not intended to denote registration or approval from the FDA.

KEEP THIS AND ALL MEDICATIONS OUT OF THE REACH OF CHILDREN.

DO NOT USE IF INNER SAFETY SEAL IS BROKEN OR MISSING.

Manufactured by: Sancilio & Company, Inc.,
Riviera Beach, FL 33404
(800) SCI-8711

© 2011 Sancilio & Company, Inc.

REV: 12/06/11

PRINCIPAL DISPLAY PANEL - 90 Tablets Bottle Label

44946-1041-5

PNV Prenatal Health
PNV
Prenatal Vitamins

FOLIC ACID + IRON
MULTIVITAMIN
Chewable
Tablets

Dispense under a
physician's order†

Dietary Supplement

Sugar Free

SCI
Sancilio & Company, Inc
Developing Good Science into Great Medicine

90
TABLETS